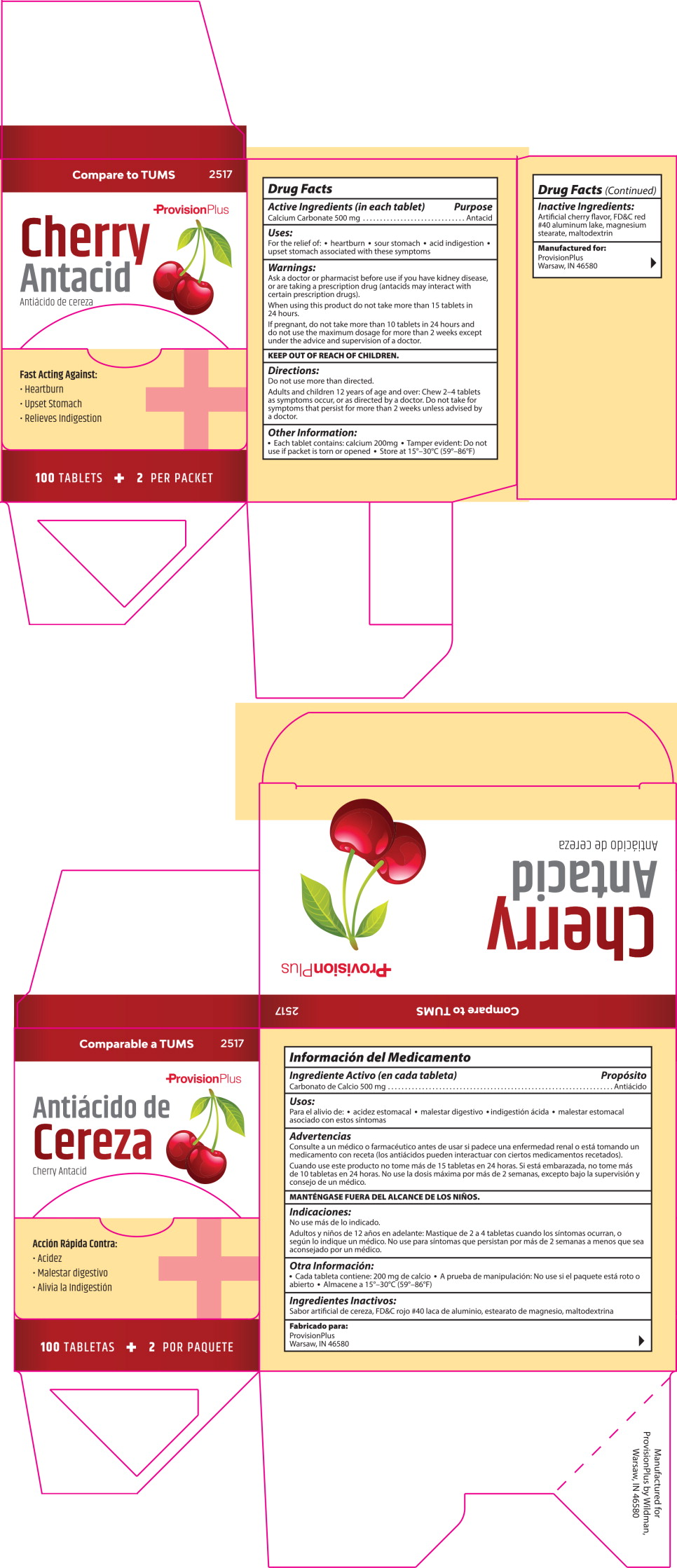 DRUG LABEL: Cherry Antacid
NDC: 84269-2517 | Form: TABLET
Manufacturer: Wildman Business Group
Category: otc | Type: HUMAN OTC DRUG LABEL
Date: 20260116

ACTIVE INGREDIENTS: Calcium Carbonate 500 mg/1 1
INACTIVE INGREDIENTS: DEXTROSE, UNSPECIFIED FORM; FD&C RED NO. 40; MAGNESIUM STEARATE; MALTODEXTRIN

Active Ingredient (in each tablet)

Calcium Carbonate 500 mg

Purpose

Antacid

Uses

For the relief of:

- heartburn
- sour stomach
- acid indigestion
- upset stomach associated with these symptoms

Warnings

Ask a doctor or pharmacist before use if you

- have kidney disease
- are taking a prescription drug. Antacids may interact with certain prescription drugs

When using this product

- do not take more than 15 tablets in 24 hours
- if pregnant, do not take more than 10 tablets in 24 hours
- do not use the maximum dosage for more than 2 weeks except under the advice and supervision of a doctor

Directions

Do not use more than directed.

adults and children 12 years of age and over:

- chew 2 – 4 tablets as symptoms occur, or as directed by a doctor
- do not take for symptoms that persist for more than 2 weeks unless advised by a doctor

Other Information

- each tablet contains: calcium 200mg
- tamper evident. Do not use if packet is torn or opened
- store at 15º-30ºC (59º-86ºF)

Inactive Ingredients

Artificial cherry flavor, FD&C red #40 aluminum lake, magnesium stearate, maltodextrin

Manufactured for:

ProvisionPlus

Warsaw, IN 46580

Principal Display Panel – 100 Tablet Box Label

Compare to TUMS 2517

ProvisionPlus

Cherry Antacid

Fast Acting Against:

- Heartburn
- Upset Stomach
- Relieves Indigestion

100 Tablets 2 Per Packet